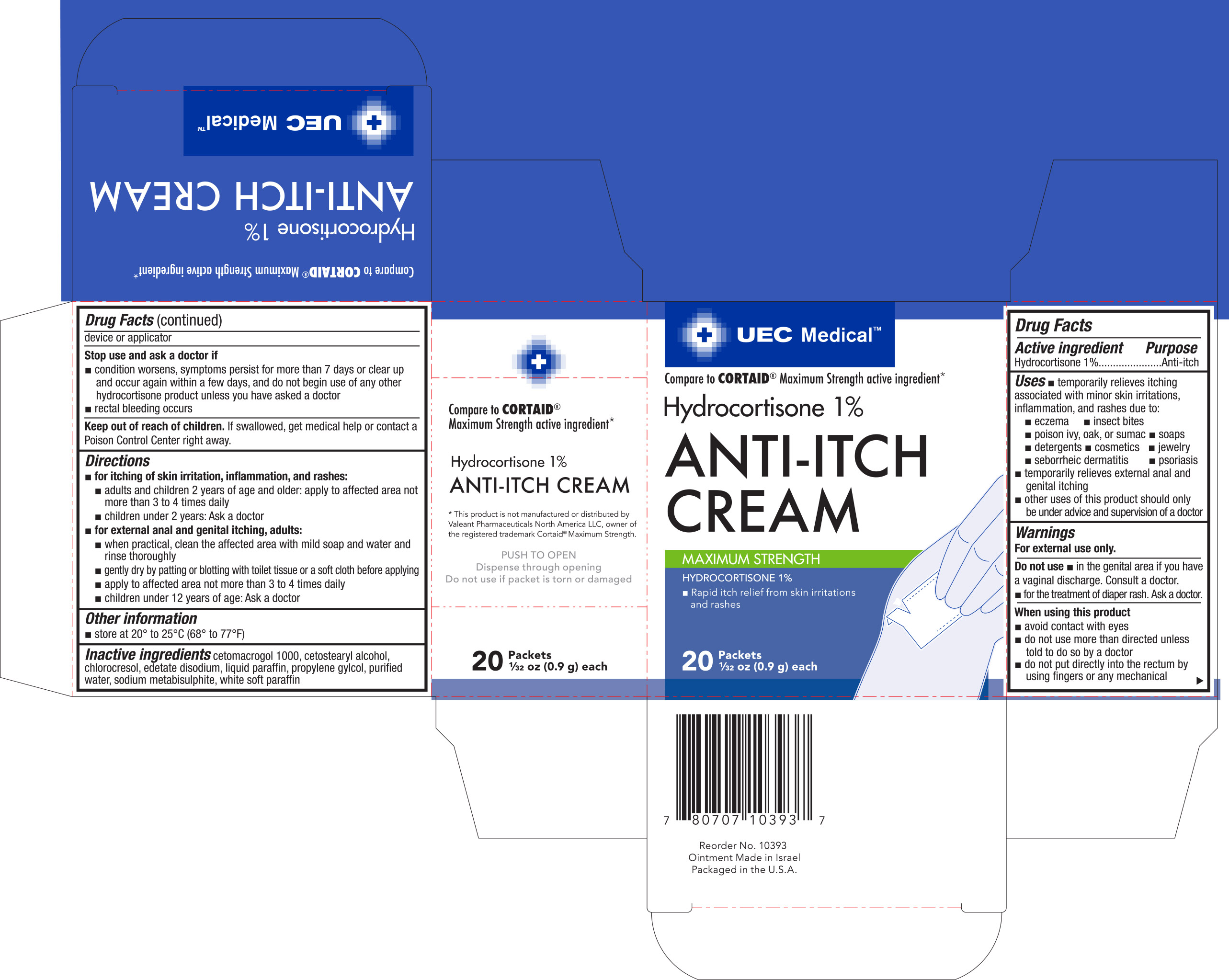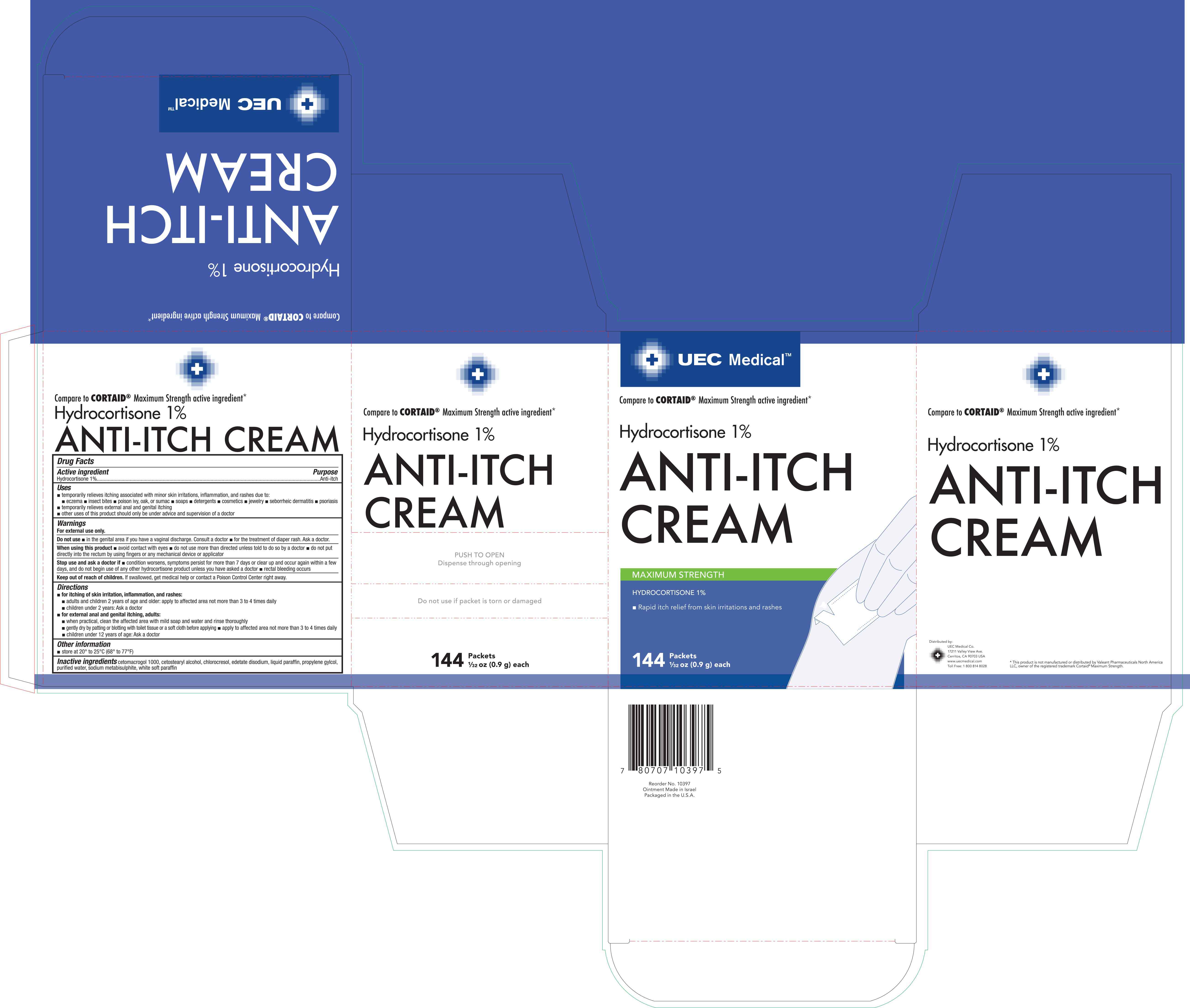 DRUG LABEL: UEC Medical Anti-Itch
NDC: 65923-393 | Form: CREAM
Manufacturer: United Exchange Corp.
Category: otc | Type: HUMAN OTC DRUG LABEL
Date: 20180405

ACTIVE INGREDIENTS: HYDROCORTISONE 1 g/100 g
INACTIVE INGREDIENTS: WATER; SODIUM METABISULFITE; PETROLATUM; PROPYLENE GLYCOL; CETETH-20; CETOSTEARYL ALCOHOL; CHLOROCRESOL; EDETATE DISODIUM; PARAFFIN

UEC Medical Hydrocortisone 1% Cream 0.9g NBE Cortaid 20 and 144 ct. - 10393 and 10397 (2018)

Active ingredient Purpose

Hydrocortisone 1%......................................................Anti-itch

Uses

- temporarily relieves itching associated with minor skin irritations, inflammation, and rashes due to:
- eczema
- insect bites
- poison ivy, oak, or sumac
- soaps
- detergents
- cosmetics
- jewelry
- seborrheic dermatitis
- psoriasis
- temporarily relieves external anal and genital itching
- other uses of this product should be under advice and supervision of a doctor

Warnings

For external use only

Do not use

- in the genital area if you have a vaginal discharge. Consult a doctor
- for the treatment of diaper rash. Ask a doctor.

When using this product

- avoid contact with eyes
- do not use more than directed unless told to do so by a doctor
- do not put directly into the rectum by using fingers or any mechanical device or applicator

Stop use and ask a doctor if

- condition worsens, symptoms persist for more than7 days or clear up and occur again within a few days, and do not begin use of any other hydrocortisone product unless you have asked a doctor
- rectal bleeding occurs

Keep out of reach of children. If swallowed, get medical help or contact a Poison Control Center right away.

Directions

- for itching of skin irritation, inflammation, and rashes:
- adults and children 2 years of age and older: apply to affected area not more than 3 to 4 times daily
- children under 2 years: Ask a doctor
- for external anal and genital itching, adults:
- when practical, clean the affected area with mild soap and water and rinse thoroughly
- gently dry by patting or blotting with toilet tissues or a soft cloth before applying
- apply to affected area not more than 3 to 4 times daily
- children under 12 years of age: Ask a doctor

Other information

- store at 20° to 25°C (68° to 77°F)

Inactive ingredients

cetamacrogol 1000, cetostearyl alcohol, chlorocresol, edetate disodium, liquid paraffin, propylene glycol, purified water, sodium metabisulphite, white soft paraffin

DOSAGE AND ADMINISTRATION

Distributed by:

Untied Exchange Corp.

17211 Valley View Ave.

Cerritos, CA 90703 USA